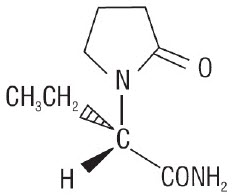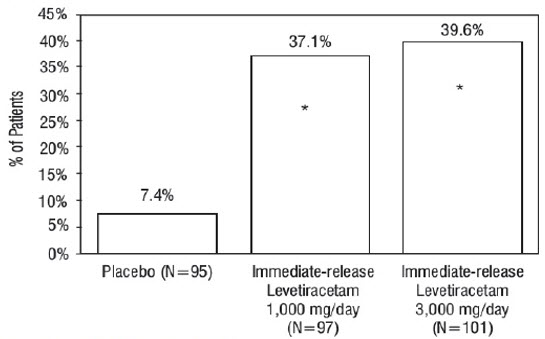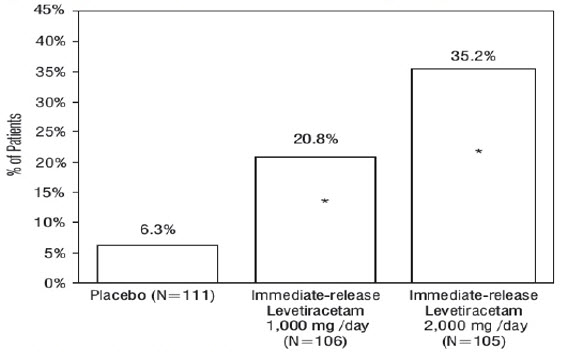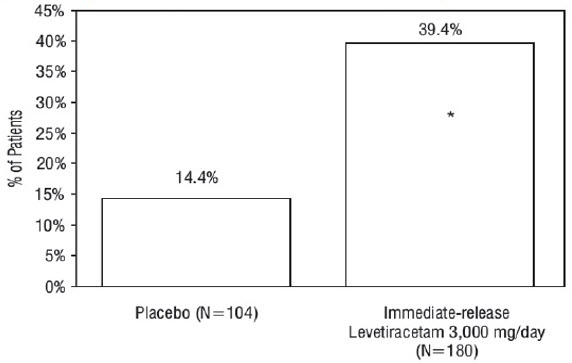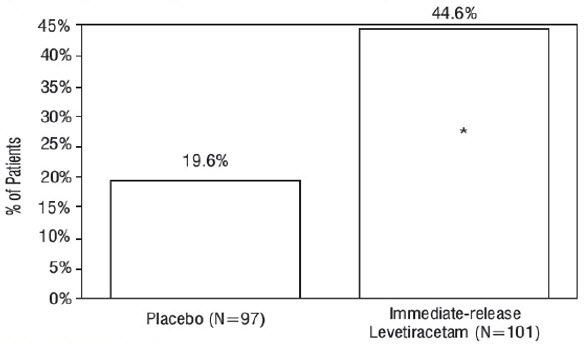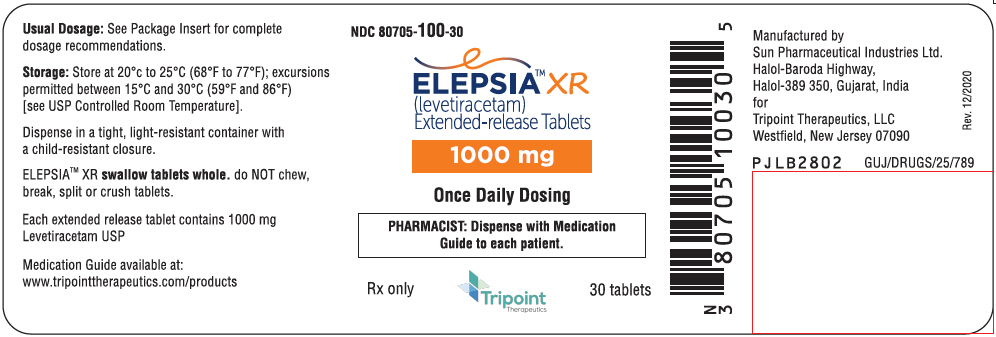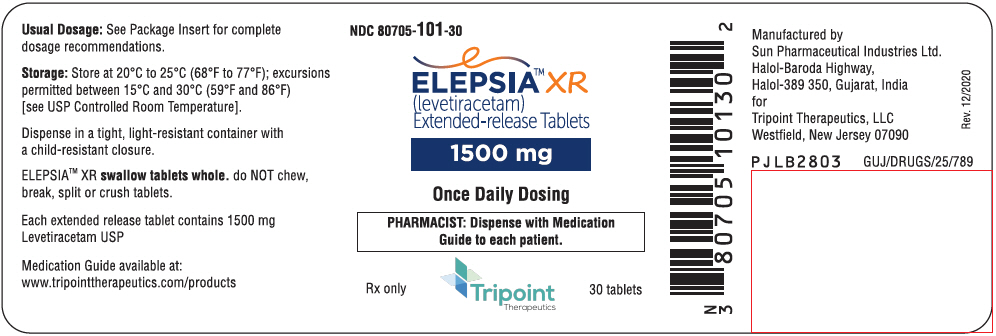 DRUG LABEL: ELEPSIA XR 1000 MG
NDC: 80705-100 | Form: TABLET, EXTENDED RELEASE
Manufacturer: TRIPOINT THERAPEUTICS, LLC
Category: prescription | Type: HUMAN PRESCRIPTION DRUG LABEL
Date: 20240325

ACTIVE INGREDIENTS: LEVETIRACETAM 1000 mg/1 1
INACTIVE INGREDIENTS: dimethylaminoethyl methacrylate - butyl methacrylate - methyl methacrylate copolymer; silicon dioxide; CROSPOVIDONE, UNSPECIFIED; dibutyl sebacate; ethylcellulose, unspecified; FD&C Blue no. 1 aluminum lake; hypromellose, unspecified; magnesium stearate; polyethylene glycol, unspecified; polysorbate 20; polysorbate 80; polyvinyl alcohol, unspecified; povidone, unspecified; sodium lauryl sulfate; talc; triethyl citrate

HIGHLIGHTS OF PRESCRIBING INFORMATION

These highlights do not include all the information needed to use ELEPSIA XR safely and effectively. See full prescribing information for ELEPSIA XR.
ELEPSIA™ XR (levetiracetam) extended-release tablets, for oral use
Initial U.S. Approval: 1999

RECENT MAJOR CHANGES

Warnings and Precautions (5.6) | 03/2024

1 INDICATIONS AND USAGE

ELEPSIA XR is indicated as adjunctive therapy for the treatment of partial-onset seizures in patients 12 years of age and older (1)

2 DOSAGE AND ADMINISTRATION

- Initiate treatment with a dose of 1000 mg once daily; increase by 1000 mg every 2 weeks to a maximum recommended dose of 3000 mg once daily (2.1)
- ELEPSIA XR should be taken whole; do not split or cut tablets (2.1)
- Not recommended for use in patients with moderate or severe renal impairment; the maximum recommended dose in patients with mild renal impairment is 2000 mg (2.2)

3 DOSAGE FORMS AND STRENGTHS

Extended-release tablets, 1000 mg, 1500 mg (3)

4 CONTRAINDICATIONS

Known hypersensitivity to levetiracetam; angioedema and anaphylaxis have occurred (4)

5 WARNINGS AND PRECAUTIONS

- Behavioral abnormalities including psychotic symptoms, suicidal ideation, irritability, and aggressive behavior have been observed; monitor patients for psychiatric signs and symptoms (5.1)
- Suicidal Behavior and Ideation: Monitor patients for new or worsening depression, suicidal thoughts/behavior, and/or unusual changes in mood or behavior (5.2)
- Monitor for somnolence and fatigue and advise patients not to drive or operate machinery until they have gained sufficient experience on ELEPSIA XR (5.3)
- Serious Dermatological Reactions: Discontinue ELEPSIA XR at the first sign of rash unless clearly not drug related (5.5)
- Drug Reaction with Eosinophilia and Systemic Symptoms (DRESS)/Multi-Organ Hypersensitivity: Discontinue if no alternative etiology (5.6)
- Coordination Difficulties: Monitor for ataxia, abnormal gait, and incoordination. Advise patients to not drive or operate machinery until they have gained experience on ELEPSIA XR (5.7)
- Withdrawal Seizures: ELEPSIA XR must be gradually withdrawn (5.8)

6 ADVERSE REACTIONS

Most common adverse reactions (incidence ≥5% more than placebo) include: somnolence and irritability (6.1)

To report SUSPECTED ADVERSE REACTIONS, contact Tripoint Therapeutics at (908) 928-4500 or FDA at 1-800-FDA-1088 or www.fda.gov/medwatch.

8 USE IN SPECIFIC POPULATIONS

Pregnancy: Plasma levels of levetiracetam may be decreased and therefore need to be monitored closely during pregnancy. Based on animal data, may cause fetal harm (5.10, 8.1)

FULL PRESCRIBING INFORMATION

1 INDICATIONS AND USAGE

ELEPSIA XR is indicated as adjunctive therapy for the treatment of partial-onset seizures in patients 12 years of age and older.

2 DOSAGE AND ADMINISTRATION

2.1 Recommended Dosing

ELEPSIA XR is administered orally once daily.

Initiate treatment with a dose of 1000 mg once daily. The once daily dosage may be adjusted in increments of 1000 mg every 2 weeks, to a maximum recommended daily dose of 3000 mg/day.

ELEPSIA XR should be taken whole; do not split or cut tablets.

2.2 Dosage Adjustment in Adult Patients with Renal Impairment

ELEPSIA XR is not recommended for use in patients with moderate or severe renal impairment. Recommended doses and adjustment for patients with mild renal impairment are shown in Table 1. In order to calculate the dose recommended for patients with renal impairment, creatinine clearance adjusted for body surface area must be calculated. To do this, an estimate of the patient's creatinine clearance (CLcr) in mL/min must first be calculated using the following formula:

CLcr = | [140-age (years)] × weight (kg) | (× 0.85 for female patients)
CLcr = | 72 × serum creatinine (mg/dL) | (× 0.85 for female patients)

Then CLcr is adjusted for body surface area (BSA) as follows:

CLcr (mL/min/1.73m^2) = | CLcr (mL/min) | × 1.73
CLcr (mL/min/1.73m^2) = | BSA subject (m^2) | × 1.73

Table 1: Dosing Adjustment Regimen for Adult Patients with Impaired Renal Function
Group | Creatinine Clearance (mL/min/1.73m^2) | Dosage (mg) | Frequency
Normal | greater than 80 | 1000 to 3000 | Every 24 hours
Mild | 50 to 80 | 1000 to 2000 | Every 24 hours

2.3 Discontinuation of ELEPSIA XR

When discontinuing ELEPSIA XR, reduce the dosage gradually and avoid abrupt discontinuation because of the risk of increased seizure frequency and status epilepticus [see Warnings and Precautions (5.8)].

3 DOSAGE FORMS AND STRENGTHS

Extended-release tablets:

- 1000 mg: oval biconvex, coated, blue and white to off-white, bilayer tablet with drilled portal on blue layer; imprinted with "574" with black ink on one side and plain on the other side.
- 1500 mg: oval biconvex, coated, blue and white to off-white, bilayer tablet with drilled portal on blue layer; imprinted with "575" with black ink on one side and plain on the other side.

4 CONTRAINDICATIONS

ELEPSIA XR is contraindicated in patients with a hypersensitivity to levetiracetam. Reactions have included anaphylaxis and angioedema [see Warnings and Precautions (5.4)].

5 WARNINGS AND PRECAUTIONS

5.1 Behavioral Abnormalities and Psychotic Symptoms

ELEPSIA XR may cause behavioral abnormalities and psychotic symptoms. Patients treated with ELEPSIA XR should be monitored for psychiatric signs and symptoms.

Behavioral Abnormalities

Levetiracetam Extended-Release Tablets

A total of 7% of levetiracetam extended-release tablets-treated patients experienced non-psychotic behavioral disorders (reported as irritability and aggression), compared to 0% of placebo-treated patients. Irritability was reported in 7% of levetiracetam extended-release tablet-treated patients. Aggression was reported in 1% of levetiracetam extended-release tablet-treated patients.

No patient discontinued treatment or had a dose reduction as a result of these adverse reactions.

The number of patients exposed to levetiracetam extended-release tablets was considerably smaller than the number of patients exposed to immediate-release levetiracetam tablets in controlled trials. Therefore, certain adverse reactions observed in the immediate-release levetiracetam controlled trials will likely to occur in patients receiving ELEPSIA XR.

Immediate-Release Levetiracetam Tablets

A total of 13% of adult patients and 38% of pediatric patients (4 to 16 years of age) treated with immediate-release levetiracetam tablets experienced non-psychotic behavioral symptoms (reported as aggression, agitation, anger, anxiety, apathy, depersonalization, depression, emotional lability, hostility, hyperkinesias, irritability, nervousness, neurosis, and personality disorder), compared to 6% and 19% of adult and pediatric patients on placebo. A randomized, double-blind, placebo-controlled study was performed to assess the neurocognitive and behavioral effects of immediate-release levetiracetam tablets as adjunctive therapy in pediatric patients (4 to 16 years of age). An exploratory analysis suggested a worsening in aggressive behavior in patients treated with immediate-release levetiracetam tablets in that study [see Use in Specific Populations (8.4)].

A total of 1.7% of adult patients treated with immediate-release levetiracetam tablets discontinued treatment due to behavioral adverse reactions, compared to 0.2% of placebo-treated patients. The treatment dose was reduced in 0.8% of adult patients treated with immediate-release levetiracetam tablets, compared to 0.5% of placebo-treated patients. Overall, 11% of pediatric patients treated with immediate-release levetiracetam tablets experienced behavioral symptoms associated with discontinuation or dose reduction, compared to 6.2% of placebo-treated pediatric patients.

One percent of adult patients and 2% of pediatric patients (4 to 16 years of age) treated with immediate-release levetiracetam tablets experienced psychotic symptoms, compared to 0.2% and 2%, respectively, in adult and pediatric placebo-treated patients. In the controlled study that assessed the neurocognitive and behavioral effects of immediate- release levetiracetam tablets in pediatric patients 4 to 16 years of age, 1.6% levetiracetam -treated patients experienced paranoia, compared to no placebo-treated patients. There were 3.1% patients treated with immediate-release levetiracetam tablets who experienced confusional state, compared to no placebo-treated patients [see Use in Specific Populations (8.4)].

Psychotic Symptoms

Immediate-Release Levetiracetam Tablets

One percent of immediate-release levetiracetam tablets-treated adult patients experienced psychotic symptoms, compared to 0.2% of placebo-treated patients.

Two (0.3%) immediate-release levetiracetam tablets-treated adult patients were hospitalized and their treatment was discontinued due to psychosis. Both events, reported as psychosis, developed within the first week of treatment and resolved within 1 to 2 weeks following treatment discontinuation. There was no difference between drug and placebo- treated patients in the incidence of pediatric patients who discontinued treatment due to psychotic and non-psychotic adverse reactions.

5.2 Suicidal Behavior and Ideation

Antiepileptic drugs (AEDs), including ELEPSIA XR, increase the risk of suicidal thoughts or behavior in patients taking these drugs for any indication. Patients treated with any AED for any indication should be monitored for the emergence or worsening of depression, suicidal thoughts or behavior, and/or any unusual changes in mood or behavior.

Pooled analyses of 199 placebo-controlled clinical trials (mono- and adjunctive therapy) of 11 different AEDs showed that patients randomized to one of the AEDs had approximately twice the risk (adjusted Relative Risk 1.8, 95% CI:1.2, 2.7) of suicidal thinking or behavior compared to patients randomized to placebo. In these trials, which had a median treatment duration of 12 weeks, the estimated incidence rate of suicidal behavior or ideation among 27,863 AED-treated patients was 0.43%, compared to 0.24% among 16,029 placebo-treated patients, representing an increase of approximately one case of suicidal thinking or behavior for every 530 patients treated. There were four suicides in drug-treated patients in the trials and none in placebo-treated patients, but the number is too small to allow any conclusion about drug effect on suicide.

The increased risk of suicidal thoughts or behavior with AEDs was observed as early as one week after starting drug treatment with AEDs and persisted for the duration of treatment assessed. Because most trials included in the analysis did not extend beyond 24 weeks, the risk of suicidal thoughts or behavior beyond 24 weeks could not be assessed.

The risk of suicidal thoughts or behavior was generally consistent among drugs in the data analyzed. The finding of increased risk with AEDs of varying mechanisms of action and across a range of indications suggests that the risk applies to all AEDs used for any indication. The risk did not vary substantially by age (5 to 100 years) in the clinical trials analyzed. Table 2 shows absolute and relative risk by indication for all evaluated AEDs.

Table 2: Risk by Indication for Antiepileptic Drugs in the Pooled Analysis
Indication | Placebo Patients with Events Per 1000 Patients | Drug Patients with Events Per 1000 Patients | Relative Risk: Incidence of Events in Drug Patients/Incidence in Placebo Patients | Risk Difference: Additional Drug Patients with Events Per 1000 Patients
Epilepsy | 1 | 3.4 | 3.5 | 2.4
Psychiatric | 5.7 | 8.5 | 1.5 | 2.9
Other | 1 | 1.8 | 1.9 | 0.9
Total | 2.4 | 4.3 | 1.8 | 1.9

The relative risk for suicidal thoughts or behavior was higher in clinical trials for epilepsy than in clinical trials for psychiatric or other conditions, but the absolute risk differences were similar for the epilepsy and psychiatric indications.

Anyone considering prescribing ELEPSIA XR or any other AED must balance the risk of suicidal thoughts or behavior with the risk of untreated illness. Epilepsy and many other illnesses for which AEDs are prescribed are themselves associated with morbidity and mortality and an increased risk of suicidal thoughts and behavior. Should suicidal thoughts and behavior emerge during treatment, the prescriber needs to consider whether the emergence of these symptoms in any given patient may be related to the illness being treated.

5.3 Somnolence and Fatigue

ELEPSIA XR may cause somnolence and fatigue. Patients should be monitored for these signs and symptoms and advised not to drive or operate machinery until they have gained sufficient experience on ELEPSIA XR to gauge whether it adversely affects their ability to drive or operate machinery.

Somnolence

Levetiracetam Extended-Release Tablets

In the levetiracetam extended-release tablets double-blind, controlled trial in patients experiencing partial-onset seizures, 8% of levetiracetam extended-release tablets-treated patients experienced somnolence, compared to 3% of placebo-treated patients.

No patient discontinued treatment or had a dose reduction as a result of these adverse reactions.

The number of patients exposed to levetiracetam extended-release tablets was considerably smaller than the number of patients exposed to immediate-release levetiracetam tablets in controlled trials. Therefore, certain adverse reactions observed in the immediate-release levetiracetam tablets controlled trials will likely occur in patients receiving ELEPSIA XR.

Immediate-Release Levetiracetam Tablets

In controlled trials of adult patients with epilepsy experiencing partial-onset seizures, 15% of immediate-release levetiracetam tablets-treated patients reported somnolence, compared to 8% of placebo treated patients. There was no clear dose response up to 3000 mg/day. In a study where there was no titration, about 45% of patients receiving 4000 mg/day (1.33 times the maximum recommended dosage) reported somnolence. The somnolence was considered serious in 0.3% of the immediate-release levetiracetam tablets-treated patients, compared to 0% in the placebo group. About 3% of immediate-release levetiracetam tablets-treated patients discontinued treatment due to somnolence, compared to 0.7% of placebo-treated patients. In 1.4% of immediate-release levetiracetam tablets-treated patients and in 0.9% of placebo-treated patients the dose was reduced, while 0.3% of the treated patients were hospitalized due to somnolence.

Asthenia

Immediate-Release Levetiracetam Tablets

In controlled trials of adult patients with epilepsy experiencing partial-onset seizures, 15% of immediate-release levetiracetam tablets-treated patients reported asthenia, compared to 9% of placebo-treated patients. Treatment was discontinued due to asthenia in 0.8% of immediate-release levetiracetam tablets-treated patients, as compared to 0.5% of placebo treated patients. In 0.5% of immediate-release levetiracetam tablets-treated patients and in 0.2% of placebo-treated patients, the dose was reduced due to asthenia.

Somnolence and asthenia occurred most frequently within the first 4 weeks of treatment.

5.4 Anaphylaxis and Angioedema

ELEPSIA XR can cause anaphylaxis or angioedema after the first dose or at any time during treatment. Signs and symptoms in cases reported in the postmarketing setting in patients treated with levetiracetam have included hypotension, hives, rash, respiratory distress, and swelling of the face, lip, mouth, eye, tongue, throat, and feet. In some reported cases, reactions were life-threatening and required emergency treatment. If a patient develops signs or symptoms of anaphylaxis or angioedema, ELEPSIA XR should be discontinued and the patient should seek immediate medical attention. ELEPSIA XR should be discontinued permanently if a clear alternative etiology for the reaction cannot be established [see Contraindications (4)].

5.5 Serious Dermatological Reactions

Serious dermatological reactions, including Stevens-Johnson syndrome (SJS) and toxic epidermal necrolysis (TEN), have been reported in patients treated with levetiracetam. The median time of onset is reported to be 14 to 17 days, but cases have been reported at least four months after initiation of treatment. Recurrence of the serious skin reactions following rechallenge with levetiracetam has also been reported. ELEPSIA XR should be discontinued at the first sign of a rash, unless the rash is clearly not drug-related. If signs or symptoms suggest SJS/TEN, use of this drug should not be resumed and alternative therapy should be considered.

5.6 Drug Reaction with Eosinophilia and Systemic Symptoms (DRESS)/Multiorgan Hypersensitivity

Drug Reaction with Eosinophilia and Systemic Symptoms (DRESS), also known as multiorgan hypersensitivity, has been reported in patients taking antiepileptic drugs, including levetiracetam. These events can be fatal or life-threatening, particularly if diagnosis and treatment do not occur as early as possible. DRESS typically, although not exclusively, presents with fever, rash, lymphadenopathy, and/or facial swelling, in association with other organ system involvement, such as hepatitis, nephritis, hematological abnormalities, myocarditis, or myositis, sometimes resembling an acute viral infection. Eosinophilia is often present. Because this disorder is variable in its expression, other organ systems not noted here may be involved. It is important to note that early manifestations of hypersensitivity, such as fever or lymphadenopathy, may be present even though rash is not evident. If such signs or symptoms are present, the patient should be evaluated immediately. ELEPSIA XR should be discontinued if an alternative etiology for the signs or symptoms cannot be established [see Contraindications (4)].

5.7 Coordination Difficulties

Coordination difficulties were not observed in the extended-release levetiracetam controlled trials, however, the number of patients exposed to levetiracetam extended-release tablets was considerably smaller than the number of patients exposed to immediate-release levetiracetam tablets in controlled trials. However, adverse reactions observed in the immediate-release levetiracetam controlled trials may also occur in patients receiving ELEPSIA XR.

Immediate-Release Levetiracetam Tablets

A total of 3.4% of adult immediate-release levetiracetam tablets-treated patients experienced coordination difficulties, (reported as either ataxia, abnormal gait, or incoordination), compared to 1.6% of placebo-treated patients. A total of 0.4% of patients in controlled trials discontinued immediate-release levetiracetam tablets treatment due to ataxia, compared to 0% of placebo-treated patients. In 0.7% of immediate-release levetiracetam tablets-treated patients and in 0.2% of placebo-treated patients, the dose was reduced due to coordination difficulties, while one of the immediate-release levetiracetam tablets-treated patients was hospitalized due to worsening of preexisting ataxia. These events occurred most frequently within the first 4 weeks of treatment.

Patients should be monitored for these signs and symptoms and advised not to drive or operate machinery until they have gained sufficient experience on ELEPSIA XR to gauge whether it could adversely affect their ability to drive or operate machinery.

5.8 Withdrawal Seizures

As with most antiepileptic drugs, ELEPSIA XR should be withdrawn gradually because of the risk of increased seizure frequency and status epilepticus [see Dosage and Administration (2.3)]. But if withdrawal is needed because of an adverse event, rapid discontinuation can be considered.

5.9 Hematologic Abnormalities

ELEPSIA XR can cause hematologic abnormalities. Hematologic abnormalities occurred in clinical trials of immediate- release levetiracetam and included decreases in white blood cells (WBC), neutrophil, and red blood cell (RBC) counts; decreases in hemoglobin and hematocrit; and increases in eosinophil counts. Cases of agranulocytosis, pancytopenia, and thrombocytopenia have also been reported in the postmarketing setting. A complete blood count is recommended in patients experiencing significant weakness, pyrexia, recurrent infections, or coagulation disorders.

Immediate-Release Levetiracetam Tablets

In controlled trials of immediate-release levetiracetam tablets in patients experiencing partial-onset seizures, minor, but statistically significant, decreases compared to placebo in total mean RBC count (0.03 × 10^6/mm^3), mean hemoglobin (0.09 g/dL), and mean hematocrit (0.38%), were seen in immediate-release levetiracetam tablets-treated patients.

A total of 3.2% of immediate-release levetiracetam tablets-treated and 1.8% of placebo-treated patients had at least one possibly significant (≤2.8 × 10^9/L) decreased WBC, and 2.4% of immediate-release levetiracetam tablets-treated and 1.4% of placebo-treated patients had at least one possibly significant (≤1.0 × 10^9/L) decreased neutrophil count. Of the immediate-release levetiracetam tablets-treated patients with a low neutrophil count, all but one rose towards or to baseline with continued treatment. No patient was discontinued secondary to low neutrophil counts.

In pediatric patients (4 to <16 years of age), statistically significant decreases in WBC and neutrophil counts were seen in patients treated with immediate-release levetiracetam tablets, as compared to placebo. The mean decreases from baseline in the immediate-release levetiracetam tablets group were -0.4 × 10^9/L and -0.3 × 10^9/L, respectively, whereas there were small increases in the placebo group. A significant increase in mean relative lymphocyte counts was observed in 1.7% of patients treated with immediate-release levetiracetam tablets compared to a decrease of 4% in patients on placebo.

In the controlled pediatric trial, a possibly clinically significant abnormal low WBC value was observed in 3% of patients treated with immediate-release levetiracetam tablets, compared to no patients on placebo. However, there was no apparent difference between treatment groups with respect to neutrophil count. No patient was discontinued secondary to low WBC or neutrophil counts.

In the controlled pediatric cognitive and neuropsychological safety study, two subjects (6.1%) in the placebo group and 5 subjects (8.6%) in the immediate-release levetiracetam tablets-treated group had high eosinophil count values that were possibly clinically significant (≥10% or ≥0.7×10^9/L).

5.10 Seizure Control During Pregnancy

Physiological changes may gradually decrease plasma levels of levetiracetam throughout pregnancy. This decrease is more pronounced during the third trimester. It is recommended that patients be monitored carefully during pregnancy. Close monitoring should continue through the postpartum period especially if the dose was changed during pregnancy.

6 ADVERSE REACTIONS

The following serious adverse reactions are discussed in more detail in other sections of labeling:

- Behavioral Abnormalities and Psychotic Symptoms [see Warnings and Precautions (5.1)]
- Suicidal Behavior and Ideation [see Warnings and Precautions (5.2)]
- Somnolence and Fatigue [see Warnings and Precautions (5.3)]
- Anaphylaxis and Angioedema [see Warnings and Precautions (5.4)]
- Serious Dermatological Reactions [see Warnings and Precautions (5.5)]
- Drug Reaction with Eosinophilia and Systemic Symptoms (DRESS)/Multiorgan Hypersensitivity [see Warnings and Precautions (5.6)]
- Coordination Difficulties [see Warnings and Precautions (5.7)]
- Hematologic Abnormalities [see Warnings and Precautions (5.9)]

6.1 Clinical Trials Experience

Because clinical trials are conducted under widely varying conditions, adverse reaction rates observed in the clinical trials of a drug cannot be directly compared to rates in the clinical trials of another drug and may not reflect the rates observed in practice.

Levetiracetam Extended-Release Tablets

In the controlled clinical study in patients with partial-onset seizures, the most common adverse reactions in patients receiving levetiracetam extended-release tablets in combination with other AEDs, for events with rates greater than placebo, were irritability and somnolence.

Table 3 lists adverse reactions that occurred in at least 5% of epilepsy patients receiving levetiracetam extended-release tablets in the placebo-controlled study and were numerically more common than in patients treated with placebo. In this study, either levetiracetam extended-release tablets or placebo was added to concurrent AED therapy.

Table 3: Adverse Reactions in the Placebo-Controlled, Add-On Study in Patients Experiencing Partial-Onset Seizures
Adverse Reactions | Levetiracetam Extended-Release Tablets (N=77) % | Placebo (N=79) %
Influenza | 8 | 4
Somnolence | 8 | 3
Irritability | 7 | 0
Nasopharyngitis | 7 | 5
Dizziness | 5 | 3
Nausea | 5 | 3

Discontinuation or Dose Reduction in the Levetiracetam Extended-Release Tablets Controlled Clinical Study

In the controlled clinical study, 5% of patients receiving levetiracetam extended-release tablets and 3% receiving placebo discontinued as a result of an adverse reaction. The adverse reactions that resulted in discontinuation and that occurred more frequently in levetiracetam extended-release tablet-treated patients than in placebo-treated patients were asthenia, epilepsy, mouth ulceration, rash, and respiratory failure. Each of these adverse reactions led to discontinuation in a levetiracetam extended-release tablet-treated patient and no placebo-treated patients.

Immediate-Release Levetiracetam Tablets

Table 4 lists the adverse reactions in the controlled studies of immediate-release levetiracetam tablets in adult patients experiencing partial-onset seizures. Although the pattern of adverse reactions in the levetiracetam extended-release tablets study seems somewhat different from that seen in partial-onset seizure controlled studies for immediate-release levetiracetam tablets, this is possibly due to the much smaller number of patients in this study compared to the immediate- release tablet studies. The adverse reactions for levetiracetam extended-release tablets are expected to be similar to those seen with immediate-release levetiracetam tablets.

Adults

In controlled clinical studies of immediate-release levetiracetam tablets as adjunctive therapy to other AEDs in adults with partial-onset seizures, the most common adverse reactions, for events with rates greater than placebo, were somnolence, asthenia, infection, and dizziness.

Table 4 lists adverse reactions that occurred in at least 1% of adult epilepsy patients receiving immediate-release levetiracetam tablets in placebo-controlled studies and were numerically more common than in patients treated with placebo. In these studies, either immediate-release levetiracetam tablets or placebo was added to concurrent AED therapy.

Table 4: Adverse Reactions in Pooled Placebo-Controlled, Add-On Studies in Adults Experiencing Partial-Onset Seizures
Adverse Reaction | Immediate-Release Levetiracetam Tablets (N=769) % | Placebo (N=439) %
Asthenia | 15 | 9
Somnolence | 15 | 8
Headache | 14 | 13
Infection | 13 | 8
Dizziness | 9 | 4
Pain | 7 | 6
Pharyngitis | 6 | 4
Depression | 4 | 2
Nervousness | 4 | 2
Rhinitis | 4 | 3
Anorexia | 3 | 2
Ataxia | 3 | 1
Vertigo | 3 | 1
Amnesia | 2 | 1
Anxiety | 2 | 1
Cough Increased | 2 | 1
Diplopia | 2 | 1
Emotional Lability | 2 | 0
Hostility | 2 | 1
Paresthesia | 2 | 1
Sinusitis | 2 | 1

Pediatric Patients 4 Years to <16 Years

In a pooled analysis of two controlled pediatric clinical studies in children 4 to 16 years of age with partial-onset seizures, the adverse reactions most frequently reported with the use of immediate-release levetiracetam tablets in combination with other AEDs, and with greater frequency than in patients on placebo, were fatigue, aggression, nasal congestion, decreased appetite, and irritability.

Table 5 lists adverse reactions that occurred in at least 2% of pediatric patients treated with immediate -release levetiracetam tablets and were more common than in pediatric patients on placebo. In these studies, either immediate-release levetiracetam tablets or placebo was added to concurrent AED therapy. Adverse reactions were usually mild to moderate in intensity.

Table 5: Adverse Reactions in Pooled Placebo-Controlled, Add-On Studies in Pediatric Patients Ages 4 to 16 Years Experiencing Partial-Onset Seizures
Adverse Reaction | Immediate-Release Levetiracetam Tablets (N=165) % | Placebo (N=131) %
Headache | 19 | 15
Nasopharyngitis | 15 | 12
Vomiting | 15 | 12
Somnolence | 13 | 9
Fatigue | 11 | 5
Aggression | 10 | 5
Abdominal Pain Upper | 9 | 8
Cough | 9 | 5
Nasal Congestion | 9 | 2
Decreased Appetite | 8 | 2
Abnormal Behavior | 7 | 4
Dizziness | 7 | 5
Irritability | 7 | 1
Pharyngolaryngeal Pain | 7 | 4
Diarrhea | 6 | 5
Lethargy | 6 | 2
Insomnia | 5 | 3
Agitation | 4 | 1
Anorexia | 4 | 3
Head Injury | 4 | 0
Constipation | 3 | 1
Contusion | 3 | 1
Depression | 3 | 1
Fall | 3 | 2
Influenza | 3 | 1
Mood Altered | 3 | 1
Affect Lability | 2 | 1
Anxiety | 2 | 1
Arthralgia | 2 | 0
Confusional State | 2 | 0
Conjunctivitis | 2 | 0
Ear Pain | 2 | 1
Gastroenteritis | 2 | 0
Joint Sprain | 2 | 1
Mood Swings | 2 | 1
Neck Pain | 2 | 1
Rhinitis | 2 | 0
Sedation | 2 | 1

In controlled pediatric clinical studies in patients 4 to 16 years of age, 7% of patients treated with immediate-release levetiracetam tablets and 9% of patients on placebo discontinued as a result of an adverse event.

In addition, the following adverse reactions were seen in other controlled studies of immediate-release levetiracetam tablets: balance disorder, disturbance in attention, eczema, hyperkinesia, memory impairment, myalgia, personality disorders, pruritus, and blurred vision.

Comparison of Gender, Age and Race

There are insufficient data for levetiracetam extended-release tablets to support a statement regarding the distribution of adverse reactions by gender, age, and race.

6.2 Postmarketing Experience

The following adverse reactions have been identified during postapproval use of immediate-release levetiracetam tablets. Because these reactions are reported voluntarily from a population of uncertain size, it is not always possible to reliably estimate their frequency or establish a causal relationship to drug exposure.

The listing is alphabetized: abnormal liver function test, acute kidney injury, anaphylaxis, angioedema, agranulocytosis, choreoathetosis, drug reaction with eosinophilia and systemic symptoms (DRESS), dyskinesia, erythema multiforme, hepatic failure, hepatitis, hyponatremia, muscular weakness, pancreatitis, pancytopenia (with bone marrow suppression identified in some of these cases), panic attack, thrombocytopenia, weight loss, and worsening of seizures. Alopecia has been reported with immediate-release levetiracetam tablet use; recovery was observed in majority of cases where immediate-release levetiracetam tablets were discontinued.

8 USE IN SPECIFIC POPULATIONS

8.1 Pregnancy

Pregnancy Exposure Registry

There is a pregnancy exposure registry that monitors pregnancy outcomes in women exposed to antiepileptic drugs (AEDs), including ELEPSIA XR, during pregnancy. Encourage women who are taking ELEPSIA XR during pregnancy to enroll in the North American Antiepileptic Drug (NAAED) pregnancy registry by calling 1-888-233-2334 or visiting http://www.aedpregnancyregistry.org/.

Risk Summary

Prolonged experience with levetiracetam in pregnant women has not identified a drug-associated risk of major birth defects or miscarriage, based on published literature, which includes data from pregnancy registries and reflects experience over two decades [see Human Data]. In animal studies, levetiracetam produced developmental toxicity (increased embryofetal and offspring mortality, increased incidences of fetal structural abnormalities, decreased embryofetal and offspring growth, neurobehavioral alterations in offspring) at doses similar to human therapeutic doses [see Animal Data].

In the U.S. general population, the estimated background risk of major birth defects and miscarriage in clinically recognized pregnancies is 2-4% and 15-20%, respectively. The background risk of major birth defects and miscarriage for the indicated population is unknown.

Clinical Considerations

Levetiracetam levels may decrease during pregnancy [see Warnings and Precautions (5.10)].

Physiological changes during pregnancy may affect levetiracetam concentration. Decrease in levetiracetam plasma concentrations has been observed during pregnancy. This decrease is more pronounced during the third trimester. Dose adjustments may be necessary to maintain clinical response.

Data

Human Data

While available studies cannot definitively establish the absence of risk, data from the published literature and pregnancy registries have not established an association with levetiracetam use during pregnancy and major birth defects or miscarriage.

Animal Data

When levetiracetam (0, 400, 1200, or 3600 mg/kg/day) was administered orally to pregnant rats during the period of organogenesis, reduced fetal weights and increased incidence of fetal skeletal variations were observed at the highest dose tested. There was no evidence of maternal toxicity. The no-effect dose for adverse effects on embryofetal development in rats (1200 mg/kg/day) is approximately 4 times the maximum recommended human dose (MRHD) of 3000 mg on a body surface area (mg/m^2) basis.

Oral administration of levetiracetam (0, 200, 600, or 1800 mg/kg/day) to pregnant rabbits during the period of organogenesis resulted in increased embryofetal mortality and incidence of fetal skeletal variations at the mid and high dose and decreased fetal weights and increased incidence of fetal malformations at the high dose, which was associated with maternal toxicity. The no-effect dose for adverse effects on embryofetal development in rabbits (200 mg/kg/day) is approximately equivalent to the MRHD on a mg/m^2 basis.

Oral administration of levetiracetam (0, 70, 350, or 1800 mg/kg/day) to female rats throughout pregnancy and lactation led to an increased incidence of fetal skeletal variations, reduced fetal body weight, and decreased growth in offspring at the mid and high doses and increased pup mortality and neurobehavioral alterations in offspring at the highest dose tested. There was no evidence of maternal toxicity. The no-effect dose for adverse effects on pre- and postnatal development in rats (70 mg/kg/day) is less than the MRHD on a mg/m^2 basis.

Oral administration of levetiracetam to rats during the latter part of gestation and throughout lactation produced no adverse developmental or maternal effects at doses of up to 1800 mg/kg/day (6 times the MRHD on a mg/m^2 basis).

8.2 Lactation

Risk Summary

Levetiracetam is excreted in human milk. There are no data on the effects of ELEPSIA XR on the breastfed infant, or the effects on milk production. The developmental and health benefits of breastfeeding should be considered along with the mother's clinical need for ELEPSIA XR and any potential adverse effects on the breastfed infant from ELEPSIA XR or from the underlying maternal condition.

8.4 Pediatric Use

Safety and effectiveness of ELEPSIA XR in pediatric patients 12 years of age and older has been established based on pharmacokinetic data in adults and adolescents using levetiracetam extended-release tablets and efficacy and safety data in controlled pediatric studies using immediate-release levetiracetam tablets [see Adverse Reactions (6.1), Clinical Pharmacology (12.3), and Clinical Studies (14.1)].

Safety and effectiveness in pediatric patients below the age of 12 years have not been established.

A 3-month, randomized, double-blind, placebo-controlled study was performed to assess the neurocognitive and behavioral effects of immediate-release levetiracetam tablets as adjunctive therapy in 98 pediatric patients with inadequately controlled partial seizures, ages 4 to 16 years (levetiracetam N=64; placebo N=34). The target dose of immediate-release levetiracetam tablets was 60 mg/kg/day. Neurocognitive effects were measured by the Leiter-R Attention and Memory (AM) Battery, which assesses various aspects of a child's memory and attention. Although no substantive differences were observed between the placebo-and levetiracetam-treated groups in the median change from baseline in this battery, the study was not adequate to assess formal statistical non-inferiority between the drug and placebo. The Achenbach Child Behavior Checklist (CBCL/6-18), a standardized validated tool used to assess a child's competencies and behavioral/emotional problems, was also assessed in this study. An analysis of the CBCL/6-18 indicated a worsening in aggressive behavior, one of the eight syndrome scores, in patients treated with levetiracetam [see Warnings and Precautions (5.1)].

Juvenile Animal Toxicity Data

Studies of levetiracetam in juvenile rats (dosing from day 4 through day 52 of age) and dogs (dosing from week 3 through week 7 of age) at doses of up to 1,800 mg/kg/day (approximately 7 and 24 times, respectively, the maximum recommended pediatric dose of 60 mg/kg/day on a mg/m^2 basis) did not indicate a potential for age-specific toxicity.

8.5 Geriatric Use

There were insufficient numbers of elderly subjects in controlled trials of epilepsy to adequately assess the effectiveness of levetiracetam extended-release tablets in these patients. It is expected that the safety of ELEPSIA XR in elderly patients 65 and over would be comparable to the safety observed in clinical studies of immediate-release levetiracetam tablets.

There were 347 subjects in clinical studies of immediate-release levetiracetam that were 65 and over. No overall differences in safety were observed between these subjects and younger subjects. There were insufficient numbers of elderly subjects in controlled trials of epilepsy to adequately assess the effectiveness of immediate-release levetiracetam tablets in these patients.

Levetiracetam is known to be substantially excreted by the kidney, and the risk of adverse reactions to this drug may be greater in patients with impaired renal function. Because elderly patients are more likely to have decreased renal function, care should be taken in dose selection, and it may be useful to monitor renal function [see Clinical Pharmacology (12.3)].

8.6 Renal Impairment

Clearance of levetiracetam is decreased in patients with renal impairment and is correlated with creatinine clearance [see Clinical Pharmacology (12.3)]. Dose adjustment is recommended for patients with mild renal impairment [see Dosage and Administration (2.2)]. ELEPSIA XR is not recommended in patients with moderate or severe renal impairment. In patients with moderate or severe renal impairment, it is recommended that lower strength levetiracetam tablets be used instead of ELEPSIA XR.

In patients with end stage renal disease on dialysis, it is recommended that immediate-release levetiracetam tablets be used instead of ELEPSIA XR.

10 OVERDOSAGE

10.1 Signs, Symptoms and Laboratory Findings of Acute Overdosage in Humans

The signs and symptoms for ELEPSIA XR overdose are expected to be similar to those seen with immediate-release levetiracetam tablets.

The highest known dose of oral immediate-release levetiracetam tablets received in the clinical development program was 6000 mg/day. Other than drowsiness, there were no adverse reactions in the few known cases of overdose in clinical trials. Cases of somnolence, agitation, aggression, depressed level of consciousness, respiratory depression and coma were observed with immediate-release levetiracetam tablet overdoses in postmarketing use.

10.2 Management of Overdose

There is no specific antidote for overdose with ELEPSIA XR. If indicated, elimination of unabsorbed drug should be attempted by emesis or gastric lavage; usual precautions should be observed to maintain airway. General supportive care of the patient is indicated including monitoring of vital signs and observation of the patient's clinical status. A Certified Poison Control Center should be contacted for up to date information on the management of overdose with ELEPSIA XR.

10.3 Hemodialysis

Standard hemodialysis procedures result in significant clearance of levetiracetam (approximately 50% in 4 hours) and should be considered in cases of overdose. Although hemodialysis has not been performed in the few known cases of overdose, it may be indicated by the patient's clinical state or in patients with significant renal impairment.

11 DESCRIPTION

ELEPSIA XR contains levetiracetam, an antiepileptic drug, as extended-release tablets for oral administration.

The chemical name of levetiracetam, a single enantiomer, is (-)-(S)-α-ethyl-2-oxo-1-pyrrolidine acetamide, its molecular formula is C8H14N2O2 and its molecular weight is 170.21. Levetiracetam is chemically unrelated to existing antiepileptic drugs (AEDs). It has the following structural formula:

Levetiracetam, USP is a white to off-white crystalline powder with a faint odor and a bitter taste. It is very soluble in water (104 g/100 mL). It is freely soluble in chloroform (65.3 g/100 mL) and in methanol (53.6 g/100 mL), soluble in ethanol (16.5 g/100 mL), sparingly soluble in acetonitrile (5.7 g/100 mL), and practically insoluble in n-hexane.

Each extended-release tablet contains 1000 mg or 1500 mg of levetiracetam. Inactive ingredients: amino methacrylate copolymer, colloidal silicon dioxide, crospovidone, dibutyl sebacate, ethyl cellulose, FD&C Blue #1 aluminum lake, hypromellose, magnesium stearate, polyethylene glycol, polysorbate 20, polysorbate 80, polyvinyl alcohol, povidone, silicified microcrystalline cellulose, sodium lauryl sulfate, talc, and triethyl citrate. The imprinting ink contains ammonium hydroxide, iron oxide black, N-butyl alcohol, propylene glycol, and shellac glaze.

ELEPSIA XR is a bilayer coated tablet. The medication is present in core of tablet and release controlling polymers are present in core and coating of tablet. The biologically inert components of core tablet and/or coating may occasionally remain intact during GI transit and may be eliminated in feces as inert fragments of coating and/or soft, hydrated mass.

12 CLINICAL PHARMACOLOGY

12.1 Mechanism of Action

The precise mechanism(s) by which levetiracetam exerts its antiepileptic effect is unknown.

A saturable and stereoselective neuronal binding site in rat brain tissue has been described for levetiracetam. Experimental data indicate that this binding site is the synaptic vesicle protein SV2A, thought to be involved in the regulation of vesicle exocytosis. Although the molecular significance of levetiracetam binding to synaptic vesicle protein SV2A is not understood, levetiracetam and related analogs showed a rank order of affinity for SV2A which correlated with the potency of their antiseizure activity in audiogenic seizure-prone mice. These findings suggest that the interaction of levetiracetam with the SV2A protein may contribute to the antiepileptic mechanism of action of the drug.

12.2 Pharmacodynamics

Effects on QTc Interval

The effects of ELEPSIA XR on QTc prolongation is expected to be the same as that of immediate-release levetiracetam tablets. The effect of immediate-release levetiracetam tablets on QTc prolongation was evaluated in a randomized, double-blind, positive-controlled (moxifloxacin 400 mg) and placebo-controlled crossover study of immediate-release levetiracetam tablets (1000 mg or 5000 mg) in 52 healthy subjects. The upper bound of the 90% confidence interval for the largest placebo-adjusted, baseline-corrected QTc was below 10 milliseconds. Therefore, there was no evidence of significant QTc prolongation in this study.

12.3 Pharmacokinetics

Overview

Bioavailability of levetiracetam extended-release tablets is similar to that of the immediate-release levetiracetam tablets. The pharmacokinetics (AUC and Cmax) were shown to be dose proportional after single dose administration of 1000 mg, 2000 mg, and 3000 mg extended-release levetiracetam. Plasma half-life of extended-release levetiracetam is approximately 7 hours. ELEPSIA XR 1500 mg tablets are bioequivalent to Keppra XR (levetiracetam) extended release tablets (2 tablets of 750 mg) in both fasted and fed states.

Levetiracetam is almost completely absorbed after oral administration. The pharmacokinetics of levetiracetam are linear and time-invariant, with low intra- and inter-subject variability. Levetiracetam is not significantly protein-bound (<10% bound) and its volume of distribution is close to the volume of intracellular and extracellular water. Sixty-six percent (66%) of the dose is renally excreted unchanged. The major metabolic pathway of levetiracetam (24% of dose) is an enzymatic hydrolysis of the acetamide group. It is not liver cytochrome P450 dependent. The metabolites have no known pharmacological activity and are renally excreted. Plasma half-life of levetiracetam across studies is approximately 6 to 8 hours. The half-life is increased in the elderly (primarily due to impaired renal clearance) and in subjects with renal impairment.

Absorption and Distribution

Extended-release levetiracetam peak plasma concentrations occur in about 4 hours. The time to peak plasma concentrations is about 3 hours longer with extended-release levetiracetam than with immediate-release tablets. After multiple dose levetiracetam extended-release tablets intake, extent of exposure (AUC0-24) was similar to extent of exposure after multiple dose immediate-release tablets intake. Cmax and Cmin were lower by 17% and 26% after multiple dose levetiracetam extended-release tablets intake in comparison to multiple dose immediate-release tablets intake. Intake of a high fat, high calorie breakfast before the administration of levetiracetam extended-release tablets resulted in a longer median time to peak. The median time to peak (Tmax) was 3 to 4.5 hours longer in the fed state. There was no effect on peak plasma concentration however; the extent of exposure (AUC) was 21 to 25% higher.

Metabolism

Levetiracetam is not extensively metabolized in humans. The major metabolic pathway is the enzymatic hydrolysis of the acetamide group, which produces the carboxylic acid metabolite, ucb L057 (24% of dose) and is not dependent on any liver cytochrome P450 isoenzymes. The major metabolite is inactive in animal seizure models. Two minor metabolites were identified as the product of hydroxylation of the 2-oxo-pyrrolidine ring (2% of dose) and opening of the 2-oxo- pyrrolidine ring in position 5 (1% of dose). There is no enantiomeric interconversion of levetiracetam or its major metabolite.

Elimination

Levetiracetam plasma half-life in adults is 7 ± 1 hour and is unaffected by either dose or repeated administration. Levetiracetam is eliminated from the systemic circulation by renal excretion as unchanged drug which represents 66% of administered dose. The total body clearance is 0.96 mL/min/kg and the renal clearance is 0.6 mL/min/kg. The mechanism of excretion is glomerular filtration with subsequent partial tubular reabsorption. The metabolite ucb L057 is excreted by glomerular filtration and active tubular secretion with a renal clearance of 4 mL/min/kg. Levetiracetam elimination is correlated to creatinine clearance. Levetiracetam clearance is reduced in patients with impaired renal function [see Dosage and Administration (2.2) and Use in Specific Populations (8.6)].

Specific Populations

Elderly

There are insufficient pharmacokinetic data to specifically address the use of extended-release levetiracetam in the elderly population.

Pharmacokinetics of immediate-release levetiracetam were evaluated in 16 elderly subjects (age 61 to 88 years) with creatinine clearance ranging from 30 to 74 mL/min. Following oral administration of twice-daily dosing for 10 days, total body clearance decreased by 38% and the half-life was 2.5 hours longer in the elderly compared to healthy adults. This is most likely due to the decrease in renal function in these subjects.

Pediatric Patients

An open label, multicenter, parallel-group, two-arm study was conducted to evaluate the pharmacokinetics of extended-release levetiracetam in pediatric patients (13 to 16 years old) and in adults (18 to 55 years old) with epilepsy.

Levetiracetam extended-release tablets (1000 mg to 3000 mg) were administered once daily with a minimum of 4 days and a maximum of 7 days of treatment to 12 pediatric patients and 13 adults in the study. Dose-normalized steady-state exposure parameters, Cmax and AUC, were comparable between pediatric and adult patients.

Pregnancy

Levetiracetam levels may decrease during pregnancy [see Warnings and Precautions (5.10) and Use in Specific Populations (8.1)].

Gender

When given in a single dose, extended-release levetiracetam Cmax was 21 to 30% higher and AUC was 8 to 18% higher in women (N=12) compared to men (N=12). However, clearances adjusted for body weight were comparable. Similar results were observed in a multiple dose study.

Race

Formal pharmacokinetic studies of the effects of race have not been conducted with extended-release or immediate-release levetiracetam. Cross study comparisons involving Caucasians (N=12) and Asians (N=12), however, show that pharmacokinetics of immediate-release levetiracetam were comparable between the two races. Because levetiracetam is primarily renally excreted and there are no important racial differences in creatinine clearance, pharmacokinetic differences due to race are not expected.

Renal Impairment

The effect of levetiracetam extended-release tablets on renally impaired patients was not assessed in the controlled study. However, it is expected that the effect on ELEPSIA XR-treated patients would be similar to that seen in controlled studies of immediate-release levetiracetam tablets.

The disposition of immediate-release levetiracetam was studied in adult subjects with varying degrees of renal function. Total body clearance of levetiracetam is reduced in patients with impaired renal function by 40% in the mild group (CLcr = 50 to 80 mL/min), 50% in the moderate group (CLcr = 30 to 50 mL/min), and 60% in the severe renal impairment group (CLcr <30 mL/min) [see Dosage and Administration (2.2) and Use in Specific Populations (8.6)]. Clearance of levetiracetam is correlated with creatinine clearance.

In anuric (end stage renal disease) patients, the total body clearance decreased 70% compared to normal subjects (CLcr >80 mL/min). Approximately 50% of the pool of levetiracetam in the body is removed during a standard 4- hour hemodialysis procedure.

Hepatic Impairment

In subjects with mild (Child-Pugh A) to moderate (Child-Pugh B) hepatic impairment, the pharmacokinetics of levetiracetam were unchanged. In patients with severe hepatic impairment (Child-Pugh C), total body clearance was 50% that of normal subjects, but decreased renal clearance accounted for most of the decrease. No dose adjustment is needed for patients with hepatic impairment.

Drug Interactions

In vitro data on metabolic interactions indicate that levetiracetam is unlikely to produce, or be subject to, pharmacokinetic interactions. Levetiracetam and its major metabolite, at concentrations well above Cmax levels achieved within the therapeutic dose range, are neither inhibitors of, nor high affinity substrates for, human liver cytochrome P450 isoforms, epoxide hydrolase, or UDP-glucuronidation enzymes. In addition, levetiracetam does not affect the in vitro glucuronidation of valproic acid.

Potential pharmacokinetic interactions of or with levetiracetam were assessed in clinical pharmacokinetic studies (phenytoin, valproate, warfarin, digoxin, oral contraceptive, probenecid) and through pharmacokinetic screening with immediate-release levetiracetam tablets in the placebo-controlled clinical studies in epilepsy patients. The potential for drug interactions for ELEPSIA XR is expected to be essentially the same as that with immediate-release levetiracetam tablets.

Phenytoin

Immediate-release levetiracetam tablets (3000 mg daily) had no effect on the pharmacokinetic disposition of phenytoin in patients with refractory epilepsy. Pharmacokinetics of levetiracetam were also not affected by phenytoin.

Valproate

Immediate-release levetiracetam tablets (1500 mg twice daily) did not alter the pharmacokinetics of valproate in healthy volunteers. Valproate 500 mg twice daily did not modify the rate or extent of levetiracetam absorption or its plasma clearance or urinary excretion. There also was no effect on exposure to and the excretion of the primary metabolite, ucb L057.

Other Antiepileptic Drugs

Potential drug interactions between immediate-release levetiracetam tablets and other AEDs (carbamazepine, gabapentin, lamotrigine, phenobarbital, phenytoin, primidone, and valproate) were also assessed by evaluating the serum concentrations of levetiracetam and these AEDs during placebo-controlled clinical studies. These data indicate that levetiracetam does not influence the plasma concentration of other AEDs and that these AEDs do not influence the pharmacokinetics of levetiracetam.

Oral Contraceptives

Immediate-release levetiracetam tablets (500 mg twice daily) did not influence the pharmacokinetics of an oral contraceptive containing 0.03 mg ethinyl estradiol and 0.15 mg levonorgestrel, or of the luteinizing hormone and progesterone levels, indicating that impairment of contraceptive efficacy is unlikely. Coadministration of this oral contraceptive did not influence the pharmacokinetics of levetiracetam.

Digoxin

Immediate-release levetiracetam tablets (1000 mg twice daily) did not influence the pharmacokinetics and pharmacodynamics (ECG) of digoxin given as a 0.25 mg dose every day. Coadministration of digoxin did not influence the pharmacokinetics of levetiracetam.

Warfarin

Immediate-release levetiracetam tablets (1000 mg twice daily) did not influence the pharmacokinetics of R and S warfarin. Prothrombin time was not affected by levetiracetam. Coadministration of warfarin did not affect the pharmacokinetics of levetiracetam.

Probenecid

Probenecid, a renal tubular secretion blocking agent, administered at a dose of 500 mg four times a day, did not change the pharmacokinetics of levetiracetam 1000 mg twice daily. Css max of the metabolite, ucb L057, was approximately doubled in the presence of probenecid while the fraction of drug excreted unchanged in the urine remained the same.

Renal clearance of ucb L057 in the presence of probenecid decreased 60%, probably related to competitive inhibition of tubular secretion of ucb L057. The effect of immediate-release levetiracetam tablets on probenecid was not studied.

13 NONCLINICAL TOXICOLOGY

13.1 Carcinogenesis, Mutagenesis, Impairment of Fertility

Carcinogenesis

Rats were dosed with levetiracetam in the diet for 104 weeks at doses of 50, 300, and 1800 mg/kg/day. Plasma exposure (AUC) at the highest dose was approximately 6 times that in humans at the maximum recommended daily human dose (MRHD) of 3000 mg. There was no evidence of carcinogenicity. In mice, oral administration of levetiracetam for 80 weeks (doses up to 960 mg/kg/day) or 2 years (doses up to 4000 mg/kg/day, lowered to 3000 mg/kg/day after 45 weeks due to intolerability) was not associated with an increase in tumors. The highest dose tested in mice for 2 years (3000 mg/kg/day) is approximately 5 times the MRHD on a body surface area (mg/m^2) basis.

Mutagenesis

Levetiracetam was negative in in vitro (Ames, chromosomal aberration in mammalian cells) and in vivo (mouse micronucleus) assays. The major human metabolite of levetiracetam (ucb L057) was negative in in vitro (Ames, mouse lymphoma) assays.

Impairment of Fertility

No adverse effects on male or female fertility or reproductive performance were observed in rats at oral doses up to 1800 mg/kg/day, which were associated with plasma exposures (AUC) up to approximately 6 times that in humans at the MRHD.

14 CLINICAL STUDIES

The efficacy of ELEPSIA XR is based upon bioavailability studies comparing levetiracetam extended-release tablets to ELEPSIA XR extended-release tablets [see Clinical Pharmacology (12.3)] and the clinical studies described below using immediate-release and extended-release levetiracetam tablets.

The effectiveness of levetiracetam extended-release tablets as adjunctive therapy in partial-onset seizures in adults was established in one multicenter, randomized, double-blind, placebo-controlled clinical study in patients who had refractory partial-onset seizures with or without secondary generalization. This was supported by the demonstration of efficacy of immediate-release levetiracetam tablets (see below) in partial seizures in three multicenter, randomized, double-blind, placebo-controlled clinical studies in adults, as well as a demonstration of comparable bioavailability between the extended-release and immediate-release formulations [see Clinical Pharmacology (12.3)] in adults. The effectiveness for levetiracetam extended-release tablets as adjunctive therapy in partial-onset seizures in pediatric patients, 12 years of age and older, was based upon a single pharmacokinetic study showing comparable pharmacokinetics of levetiracetam extended-release tablets in adults and adolescents [see Clinical Pharmacology (12.3)]. All studies are described below.

14.1 Levetiracetam Extended-Release Tablets in Adults

The effectiveness of levetiracetam extended-release tablets as adjunctive therapy (added to other antiepileptic drugs) was established in one multicenter, randomized, double-blind, placebo-controlled clinical study across 7 countries in patients who had refractory partial-onset seizures with or without secondary generalization (Study 1).

Study 1

Patients enrolled in Study 1 had at least eight partial seizures with or without secondary generalization during the 8-week baseline period and at least two partial seizures in each 4-week interval of the baseline period. Patients were taking a stable dose regimen of at least one AED, and could take a maximum of three AEDs. After a prospective baseline period of 8 weeks, 158 patients were randomized to placebo (N=79) or 1000 mg (two 500 mg tablets) of levetiracetam extended- release tablets (N=79), given once daily over a 12-week treatment period.

The primary efficacy endpoint in Study 1 was the percent reduction over placebo in mean weekly frequency of partial- onset seizures. The median percent reduction in weekly partial-onset seizure frequency from baseline over the treatment period was 46.1% in the levetiracetam extended-release tablets 1000 mg treatment group (N=74) and 33.4% in the placebo group (N=78). The estimated percent reduction over placebo in weekly partial-onset seizure frequency over the treatment period was 14.4% (statistically significant).

The relationship between the effectiveness of the same daily dose of levetiracetam extended-release tablets and immediate-release levetiracetam tablets has not been studied and is unknown.

14.2 Immediate-Release Levetiracetam Tablets in Adults

The effectiveness of immediate-release levetiracetam as adjunctive therapy (added to other antiepileptic drugs) in adults was established in three multicenter, randomized, double-blind, placebo-controlled clinical studies in patients who had refractory partial-onset seizures with or without secondary generalization (Studies 2, 3, and 4). The tablet formulation was used in all three studies. In these studies, 904 patients were randomized to placebo, levetiracetam 1000 mg, levetiracetam 2000 mg, or levetiracetam 3000 mg/day. Patients enrolled in Study 2 or Study 3 had refractory partial-onset seizures for at least two years, and had taken two or more AEDs. Patients enrolled in Study 4 had refractory partial-onset seizures for at least 1 year and had taken one AED. At the time of the study, patients were taking a stable dose regimen of at least one AED, and could take a maximum of two AEDs. During the baseline period, patients had to have experienced at least two partial-onset seizures during each 4-week period.

Study 2

Study 2 was a double-blind, placebo-controlled, parallel-group study conducted at 41 sites in the United States, comparing immediate-release levetiracetam 1000 mg/day (N=97), immediate-release levetiracetam 3000 mg/day (N=101), and placebo (N=95), given in equally divided doses twice daily. After a prospective baseline period of 12 weeks, patients in Study 2 were randomized to one of the three treatment groups described above. The 18-week treatment period consisted of a 6-week titration period, followed by a 12-week fixed dose evaluation period, during which concomitant AED regimens were held constant. The primary measure of effectiveness in Study 2 was a between-group comparison of the percent reduction in weekly partial seizure frequency relative to placebo over the entire randomized treatment period (titration + evaluation period). Secondary outcome variables included the responder rate (incidence of patients with ≥50% reduction from baseline in partial-onset seizure frequency). The results of Study 2 are displayed in Table 6.

Table 6: Reduction in Mean Over Placebo in Weekly Frequency of Partial-Onset Seizures in Study 2
 | Placebo (N=95) | Immediate-release Levetiracetam 1,000 mg/day (N=97) | Immediate-release Levetiracetam 3,000 mg/day (N=101)
Percent reduction in partial seizure frequency over placebo | – | 26.1% [statistically significant versus placebo] | 30.1%

The percentage of patients (y-axis) who achieved ≥50% reduction from baseline in weekly partial-onset seizure frequency over the entire randomized treatment period (titration + evaluation period) within the three treatment groups (x-axis) in Study 2 is presented in Figure 1.

Figure 1: Responder Rate (≥50% Reduction From Baseline) In Study 2

* statistically significant versus placebo

Study 3

Study 3 was a double-blind, placebo-controlled, crossover study conducted at 62 centers in Europe, comparing immediate-release levetiracetam 1000 mg/day (N=106), immediate-release levetiracetam 2000 mg/day (N=105), and placebo (N=111), given in equally divided doses twice daily.

The first period of the study (Period A) was designed to be analyzed as a parallel-group study. After a prospective baseline period of up to 12 weeks, patients in Study 3 were randomized to one of the three treatment groups described above. The 16-week treatment period consisted of the 4-week titration period followed by a 12-week fixed dose evaluation period, during which concomitant AED regimens were held constant. The primary measure of effectiveness in Study 3 was a between group comparison of the percent reduction in weekly partial seizure frequency relative to placebo over the entire randomized treatment period (titration + evaluation period). Secondary outcome variables included the responder rate (incidence of patients with ≥50% reduction from baseline in partial-onset seizure frequency). The results of the analysis of Period A are displayed in Table 7.

Table 7: Reduction in Mean Over Placebo in Weekly Frequency of Partial-Onset Seizures in Study 3: Period A
 | Placebo (N=111) | Immediate-release Levetiracetam 1000 mg/day (N=106) | Immediate-release Levetiracetam 2000 mg/day (N=105)
Percent reduction in partial seizure frequency over placebo | – | 17.1% [statistically significant versus placebo] | 21.4%

The percentage of patients (y-axis) who achieved ≥50% reduction from baseline in weekly partial-onset seizure frequency over the entire randomized treatment period (titration + evaluation period) within the three treatment groups (x-axis) in Study 3 is presented in Figure 2.

Figure 2: Responder Rate (≥50% Reduction From Baseline) In Study 3: Period A

* statistically significant versus placebo

The comparison of immediate-release levetiracetam 2000 mg/day to immediate-release levetiracetam 1000 mg/day for responder rate in Study 3 was statistically significant (P=0.02). Analysis of the trial as a cross-over study yielded similar results.

Study 4

Study 4 was a double-blind, placebo-controlled, parallel-group study conducted at 47 centers in Europe comparing immediate-release levetiracetam 3000 mg/day (N=180) and placebo (N=104) in patients with refractory partial-onset seizures, with or without secondary generalization, receiving only one concomitant AED. Study drug was given in two divided doses. After a prospective baseline period of 12 weeks, patients in Study 4 were randomized to one of two treatment groups described above. The 16-week treatment period consisted of a 4-week titration period, followed by a 12- week fixed dose evaluation period, during which concomitant AED doses were held constant. The primary measure of effectiveness in Study 4 was a between group comparison of the percent reduction in weekly seizure frequency relative to placebo over the entire randomized treatment period (titration + evaluation period). Secondary outcome variables included the responder rate (incidence of patients with ≥50% reduction from baseline in partial-onset seizure frequency). Table 8 displays the results of Study 4.

Table 8: Reduction in Mean Over Placebo in Weekly Frequency of Partial-Onset Seizures in Study 4
 | Placebo (N=104) | Immediate-release Levetiracetam 3000 mg/day (N=180)
Percent reduction in partial seizure frequency over placebo | – | 23% [statistically significant versus placebo]

The percentage of patients (y-axis) who achieved ≥50% reduction from baseline in weekly partial-onset seizure frequency over the entire randomized treatment period (titration + evaluation period) within the two treatment groups (x-axis) in Study 4 is presented in Figure 3.

Figure 3: Responder Rate (≥50% Reduction From Baseline) In Study 4

14.3 Immediate-Release Levetiracetam in Pediatric Patients 4 Years to 16 Years

The use of levetiracetam extended-release tablets in pediatric patients 12 years of age and older is supported by Study 5, which was conducted using immediate-release levetiracetam. ELEPSIA XR is not indicated in pediatric patients below 12 years of age.

Study 5

The effectiveness of immediate-release levetiracetam as adjunctive therapy in pediatric patients was established in a multicenter, randomized double-blind, placebo-controlled study, conducted at 60 sites in North America, in children 4 to 16 years of age with partial seizures uncontrolled by standard antiepileptic drugs (Study 5). Eligible patients on a stable dose of 1 to 2 AEDs, who still experienced at least 4 partial-onset seizures during the 4 weeks prior to screening, as well as at least 4 partial-onset seizures in each of the two 4-week baseline periods, were randomized to receive either immediate-release levetiracetam or placebo. The enrolled population included 198 patients (levetiracetam N=101; placebo N=97) with refractory partial-onset seizures, with or without secondarily generalization. Study 5 consisted of an 8-week baseline period and 4-week titration period followed by a 10-week evaluation period. Dosing was initiated at a dose of 20 mg/kg/day in two divided doses. During the treatment period, the immediate-release levetiracetam doses were adjusted in 20 mg/kg/day increments, at 2-week intervals to the target dose of 60 mg/kg/day. The primary measure of effectiveness in Study 5 was a between group comparison of the percent reduction in weekly partial seizure frequency relative to placebo over the entire 14-week randomized treatment period (titration + evaluation period). Secondary outcome variables included the responder rate (incidence of patients with ≥ 50% reduction from baseline in partial-onset seizure frequency per week). Table 9 displays the results of this study.

Table 9: Reduction in Mean Over Placebo in Weekly Frequency of Partial-Onset Seizures in Study 5
 | Placebo (N=97) | Immediate-release Levetiracetam (N=101)
Percent reduction in partial seizure frequency over placebo | – | 26.8% [statistically significant versus placebo]

The percentage of patients (y-axis) who achieved ≥ 50% reduction in weekly partial-onset seizure frequency over the entire randomized treatment period (titration + evaluation period) within the two treatment groups (x-axis) in Study 5 is presented in Figure 4.

Figure 4: Responder Rate (≥ 50% Reduction From Baseline) In Study 5

* statistically significant versus placebo

16 HOW SUPPLIED/STORAGE AND HANDLING

16.1 How Supplied

ELEPSIA XR tablets, 1000 mg are oval biconvex, coated, blue and white to off-white, bilayer tablet with drilled portal on the blue layer; imprinted with "574" with black ink on one side and plain on the other side. They are supplied as follows:

Bottles of 30 with child resistant cap | NDC 80705-100-30
Blister of 7 as a physician sample | NDC 80705-100-99
Blister of 2 as a physician sample | NDC 80705-100-02

ELEPSIA XR tablets, 1500 mg are oval biconvex, coated, blue and white to off-white, bilayer tablet with drilled portal on the blue layer; imprinted with "575" with black ink on one side and plain on the other side. They are supplied as follows:

Bottles of 30 with child resistant cap | NDC 80705-101-30
Blister of 7 as a physician sample | NDC 80705-101-99
Blister of 2 as a physician sample | NDC 80705-101-02

16.2 Storage and Handling

Store at 20°C to 25°C (68°F to 77°F); excursions permitted between 15°C and 30°C (59°F and 86°F) [see USP Controlled Room Temperature]. Dispense in tight, light-resistant container.

17 PATIENT COUNSELING INFORMATION

Advise the patient to read the FDA-approved Patient Labeling (Medication Guide).

Psychiatric Reactions and Changes in Behavior

Advise patients that ELEPSIA XR may cause changes in behavior (e.g. irritability and aggression). In addition, patients should be advised that they may experience changes in behavior that have been seen with other formulations of levetiracetam, which include agitation, anger, anxiety, apathy, depression, hostility, psychotic symptoms [see Warnings and Precautions (5.1)].

Suicidal Behavior and Ideation

Counsel patients, their caregivers, and/or families that antiepileptic drugs (AEDs), including ELEPSIA XR, may increase the risk of suicidal thoughts and behavior and advise patients to be alert for the emergence or worsening of symptoms of depression; unusual changes in mood or behavior; or suicidal thoughts, behavior, or thoughts about self-harm. Advise patients, their caregivers, and/or families to immediately report behaviors of concern to a healthcare provider [see Warnings and Precautions (5.2)].

Effects on Driving or Operating Machinery

Inform patients that ELEPSIA XR may cause dizziness and somnolence. Inform patients not to drive or operate machinery until they have gained sufficient experience on ELEPSIA XR to gauge whether it adversely affects their ability to drive or operate machinery [see Warnings and Precautions (5.3)].

Anaphylaxis and Angioedema

Advise patients to discontinue ELEPSIA XR and seek medical care if they develop signs and symptoms of anaphylaxis or angioedema [see Warnings and Precautions (5.4)].

Dermatological Adverse Reactions

Advise patients that serious dermatological adverse reactions have occurred in patients treated with levetiracetam and instruct them to call their physician immediately if a rash develops [see Warnings and Precautions (5.5)].

DRESS/Multi-organ Hypersensitivity

Instruct patients and caregivers that a fever or rash associated with signs of other organ system involvement (e.g., lymphadenopathy, hepatic dysfunction) may be drug-related and should be reported to their healthcare provider immediately. ELEPSIA XR should be discontinued immediately if a serious hypersensitivity reaction is suspected [see Warnings and Precautions (5.6)].

Dosing and Administration

Patients should be instructed to only take ELEPSIA XR once daily and to swallow the tablets whole. The tablet should not be chewed, broken, or crushed [see Dosage and Administration (2.1)]. Inform patients that they should not be concerned if they occasionally notice something that looks like inert fragments of coating and/or swollen pieces of the original tablet in their stool.

Each coated bilayer tablet consists of a distinctly visible blue layer and a white to off white layer. Do not consume the tablet if one layer is absent and report this to your pharmacist [see Dosage Forms and Strengths (3)].

Pregnancy

Advise patients to notify their healthcare provider if they become pregnant or intend to become pregnant during ELEPSIA XR therapy. Encourage patients to enroll in the North American Antiepileptic Drug (NAAED) pregnancy registry if they become pregnant. This registry is collecting information about the safety of antiepileptic drugs during pregnancy [see Use in Specific Populations (8.1)].

Rx Only

Manufactured by
Sun Pharmaceutical Industries Ltd.
Halol-Baroda Highway
Halol-389 350, Gujarat, India

Manufactured for
Tripoint Therapeutics, LLC
Westfield, NJ 07090

Copyright 2020, Tripoint Therapeutics LLC
All rights reserved
03/2024

uspi-ELEPSIA-XR-tab-00002

MEDICATION GUIDE

ELEPSIA™ XR (e lep' see a ex are)
(levetiracetam)
extended-release tablets, for oral use

Read this Medication Guide before you start taking ELEPSIA XR and each time you get a refill. There may be new information. This information does not take the place of talking to your healthcare provider about your medical condition or treatment.

What is the most important information I should know about ELEPSIA XR?

Like other antiepileptic drugs, ELEPSIA XR may cause suicidal thoughts or actions in a very small number of people, about 1 in 500 people taking it.

Call a healthcare provider right away if you have any of these symptoms, especially if they are new, worse, or worry you:

- thoughts about suicide or dying
- attempts to commit suicide
- new or worse depression
- new or worse anxiety
- feeling agitated or restless
- panic attacks
- trouble sleeping (insomnia)
- new or worse irritability
- acting aggressive, being angry, or violent
- acting on dangerous impulses
- an extreme increase in activity and talking (mania)
- other unusual changes in behavior or mood

Do not stop ELEPSIA XR without first talking to a healthcare provider.

- Stopping ELEPSIA XR suddenly can cause serious problems. Stopping a seizure medicine suddenly can cause seizures that will not stop (status epilepticus).
- Suicidal thoughts or actions can be caused by things other than medicines. If you have suicidal thoughts or actions, your healthcare provider may check for other causes.

How can I watch for early symptoms of suicidal thoughts and actions?

- Pay attention to any changes, especially sudden changes, in mood, behaviors, thoughts, or feelings.
- Keep all follow-up visits with your healthcare provider as scheduled.

Call your healthcare provider between visits as needed, especially if you are worried about symptoms.

What is ELEPSIA XR?

ELEPSIA XR is a prescription medicine taken by mouth that is used with other medicines to treat partial onset seizures in people 12 years of age and older.

It is not known if ELEPSIA XR is safe or effective in people under 12 years of age.

Who should not take ELEPSIA XR?

Do not take ELEPSIA XR if you are allergic to levetiracetam.

What should I tell my healthcare provider before starting ELEPSIA XR?

Before taking ELEPSIA XR, tell your healthcare provider about all of your medical conditions, including if you:

- have or have had depression, mood problems or suicidal thoughts or behavior.
- have kidney problems.
- are pregnant or planning to become pregnant. It is not known if ELEPSIA XR will harm your unborn baby. You and your healthcare provider will have to decide if you should take ELEPSIA XR while you are pregnant. If you become pregnant while taking ELEPSIA XR, talk to your healthcare provider about registering with the North American Antiepileptic Drug Pregnancy Registry. You can enroll in this registry by calling 1-888-233-2334 or go to http://www.aedpregnancyregistry.org. The purpose of this registry is to collect information about the safety of ELEPSIA XR and other antiepileptic medicines during pregnancy.
- are breastfeeding or plan to breastfeed. ELEPSIA XR can pass into your breast milk. It is not known if the ELEPSIA XR that passes into your breast milk can harm your baby. Talk to your healthcare provider about the best way to feed your baby while you receive ELEPSIA XR.

Tell your healthcare provider about all the medicines you take, including prescription and over -the-counter medicines, vitamins, and herbal supplements. Do not start a new medicine without first talking with your healthcare provider.

Know the medicines you take. Keep a list of them to show your healthcare provider and pharmacist each time you get a new medicine.

How should I take ELEPSIA XR?

Take ELEPSIA XR exactly as your healthcare provider tells you take it.

- Your healthcare provider will tell you how much ELEPSIA XR to take and when to take it. ELEPSIA XR is usually taken 1 time per day.
- Your healthcare provider may change your dose. Do not change your dose without talking to your healthcare provider.
- Swallow the tablets whole. Do not chew, cut, break, split or crush tablets.
- Each coated tablet has 2 layers, a blue layer and a white to off-white layer. If you do not see the blue or white off- white layer, do not take the tablet and talk to your pharmacist.
- The inactive part of ELEPSIA XR tablets may not dissolve after all the medicine has been released in your body. You may sometimes notice something in your bowel movement that looks like pieces of coating or swollen pieces of the original tablet. This is normal.
- If you take too much ELEPSIA XR, call your local Poison Control Center or go to the nearest emergency room right away.

What should I avoid while taking ELEPSIA XR?

Do not drive, operate machinery or do other dangerous activities until you know how ELEPSIA XR affects you. ELEPSIA XR may make you dizzy or sleepy.

What are the possible side effects of ELEPSIA XR?

See "What is the most important information I should know about ELEPSIA XR?"

Call your healthcare provider right away if you have any of these symptoms:

- mood and behavior changes such as aggression, agitation, anger, anxiety, apathy, mood swings, depression, hostility, and irritability. A few people may get psychotic symptoms such as hallucinations (seeing or hearing things that are really not there), delusions (false or strange thoughts or beliefs) and unusual behavior.
- extreme sleepiness, tiredness, and weakness
- problems with muscle coordination (problems walking and moving)
- allergic reactions such as swelling of the face, lips, eyes, tongue, and throat, trouble swallowing or breathing, and hives.
- a skin rash. Serious skin rashes can happen after you start taking ELEPSIA XR. There is no way to tell if a mild rash will become a serious reaction.
- a serious allergic reaction that may affect your skin or other parts of your body such as your liver, kidneys, heart, or blood cells. This allergic reaction can be life-threatening and can cause death, particularly if it is not treated as early as possible. Call your healthcare provider right away if you have:
  - a skin rash
  - fever or swollen glands that do not go away
  - swelling of your face
  - shortness of breath
  - yellowing of the skin or whites of the eyes
  - dark urine

Common side effects seen in people who take ELEPSIA XR:

- flu
- sleepiness
- irritability
- nasal congestion, sore throat, and runny nose (nasopharyngitis)
- dizziness
- nausea

Tell your healthcare provider if you have any side effect that bothers you or that does not go away.

These are not all the possible side effects of ELEPSIA XR. For more information, ask your healthcare provider or pharmacist.

Call your doctor for medical advice about side effects. You may report side effects to FDA at 1-800-FDA-1088.

How should I store ELEPSIA XR?

Store ELEPSIA XR at room temperature, between 68°F to 77°F (20°C to 25°C) away from light.

Keep ELEPSIA XR and all medicines out of the reach of children.

General information about the safe and effective use of ELEPSIA XR.

Medicines are sometimes prescribed for purposes other than those listed in a Medication Guide. Do not use ELEPSIA XR for a condition for which it was not prescribed. Do not give ELEPSIA XR to other people, even if they have the same symptoms that you have. It may harm them.

You can ask your pharmacist or healthcare provider for information about ELEPSIA XR that is written for health professionals.

What are the ingredients of ELEPSIA XR?

Active ingredient: levetiracetam

Inactive ingredients: amino methyacrylate copolymer, colloidal silicon dioxide, crospovidone, dibutyl sebacate, ethyl cellulose, FD&C Blue #1 aluminum lake, hypromellose, magnesium stearate, polyethylene glycol, polysorbate 20, polysorbate 80, polyvinyl alcohol, povidone, silicified microcrystalline cellulose, sodium lauryl sulfate, talc, and triethyl citrate. The imprinting ink contains ammonium hydroxide, iron oxide black, N-butyl alcohol, propylene glycol, and shellac glaze.

Rx Only

Manufactured by
Sun Pharmaceutical Industries Ltd.
Halol-Baroda Highway,
Halol-389 350, Gujarat, India

Manufactured for
Tripoint Therapeutics, LLC
Westfield, New Jersey
07090

Copyright 2020, Tripoint Therapeutics LLC
All rights reserved

For more information, call Tripoint Therapeutics at (908) 928-4500.

This Medication Guide has been approved by the U.S. Food and Drug Administration.

Revised: 03/2024

PRINCIPAL DISPLAY PANEL - 1000 mg Tablet Bottle Label

NDC 80705-100-30

ELEPSIA™ XR
(levetiracetam)
Extended-release Tablets

1000 mg

Once Daily Dosing

PHARMACIST: Dispense with Medication
Guide to each patient.

Rx only

Tripoint
Therapeutics

30 tablets

PRINCIPAL DISPLAY PANEL - 1500 mg Tablet Bottle Label

NDC 80705-101-30

ELEPSIA™ XR
(levetiracetam)
Extended-release Tablets

1500 mg

Once Daily Dosing

PHARMACIST: Dispense with Medication
Guide to each patient.

Rx only

Tripoint
Therapeutics

30 tablets